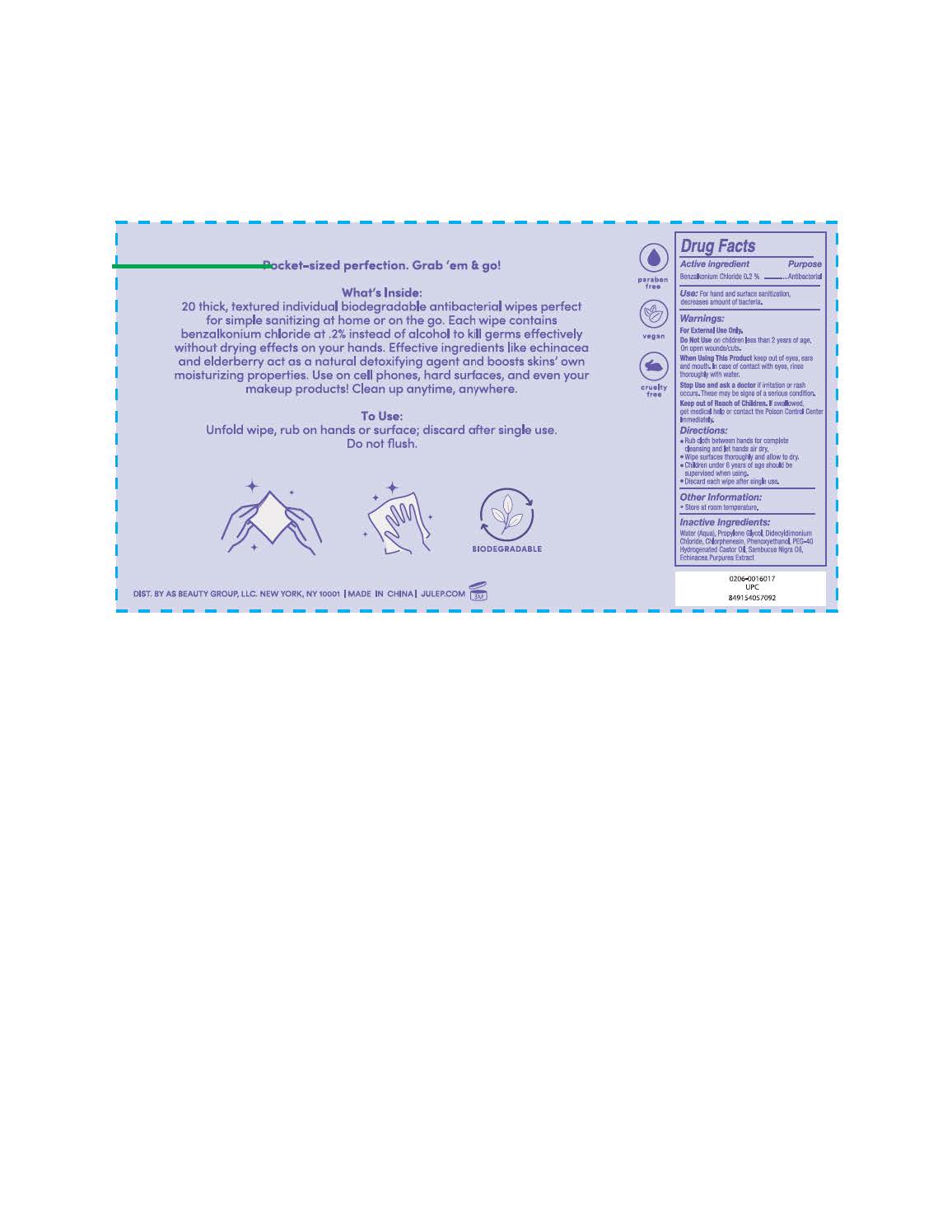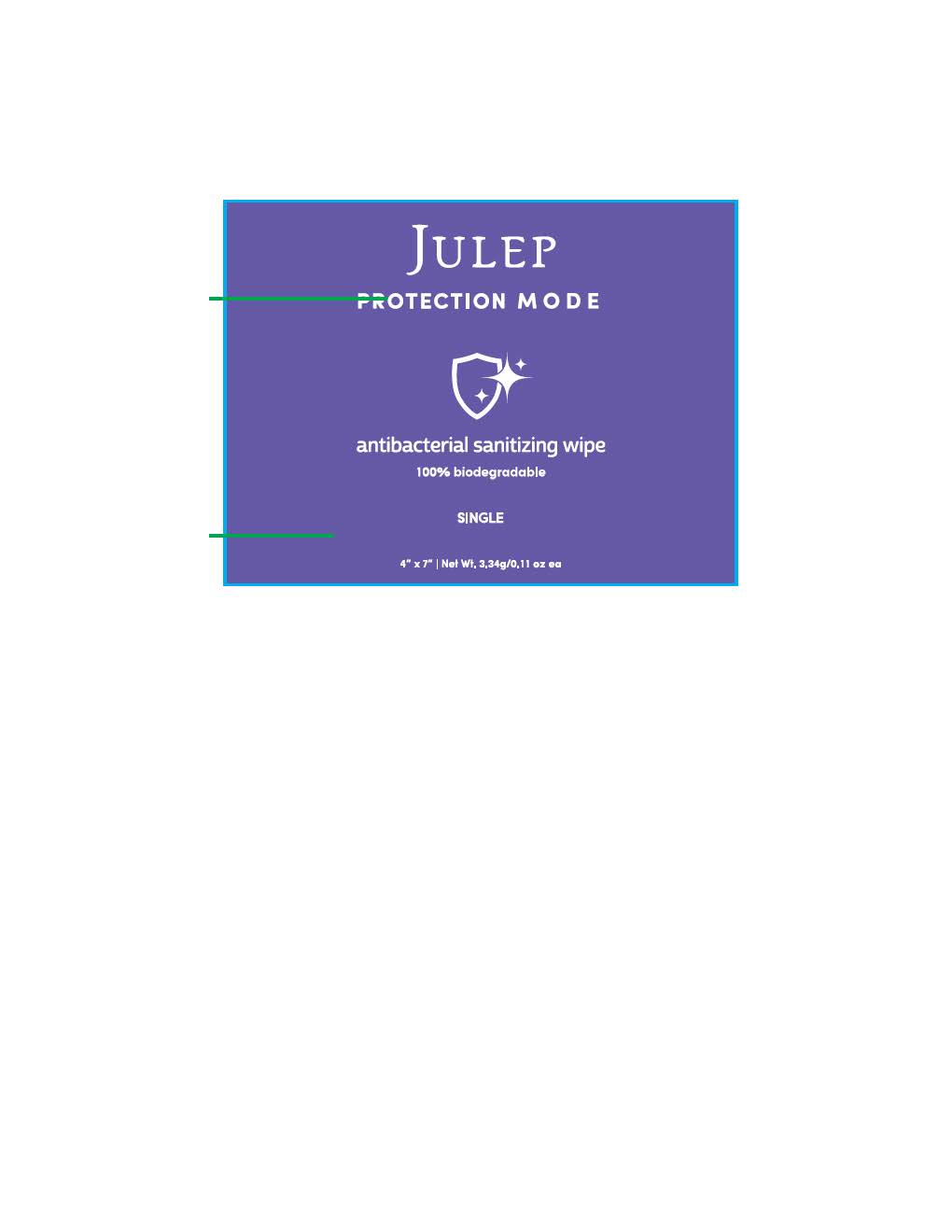 DRUG LABEL: Antibacterial Hand Wipes
NDC: 74884-121 | Form: CLOTH
Manufacturer: AS Beauty
Category: otc | Type: HUMAN OTC DRUG LABEL
Date: 20200915

ACTIVE INGREDIENTS: BENZALKONIUM CHLORIDE 0.2 g/0.2 g
INACTIVE INGREDIENTS: DIDECYLDIMONIUM CHLORIDE; POLYOXYL 40 HYDROGENATED CASTOR OIL; SAMBUCUS NIGRA SEED OIL; CHLORPHENESIN; PHENOXYETHANOL; ECHINACEA PURPUREA; WATER

Antibacterial Wipe

How To Use

Rub cloth between both hands thouroughly, and let air dry.

Non Active Ingredients.

Inactive Ingredients Water (Aqua), Propylene Glycol, Didecyldimonium Chloride, Chlorphenesin, Phenoxyethanol, PEG-40 Hydrogenated Castor Oil, Sambucus Nigra Oil, Echinacea Purpurea Extract

Usage Indications

Stop using Wipes if rash or irritation occurs.

Keep Out Of Reach of Children

Actives Purpose

Antibacterial

Warnings

For External Use Only. Keep Out of Eyes, Ears, and Mouth. Do not use on open wounds or cuts.